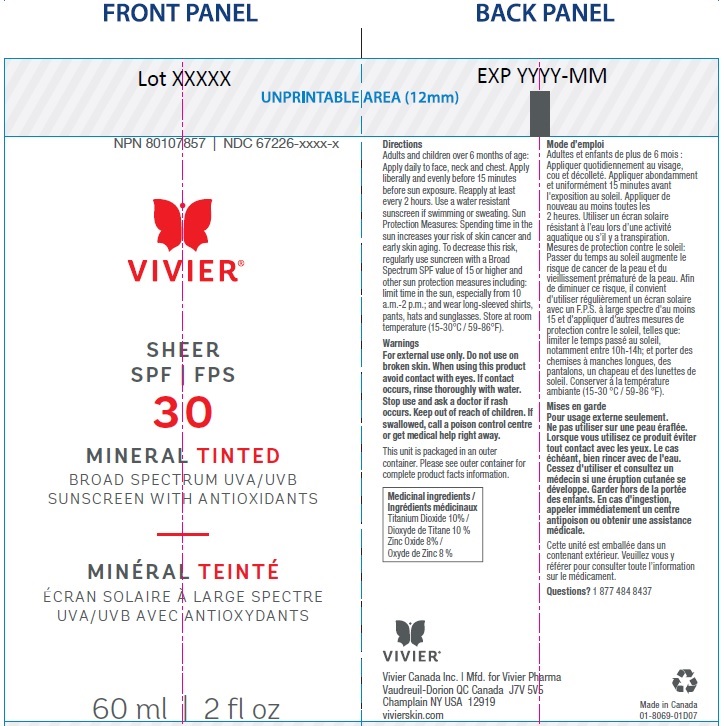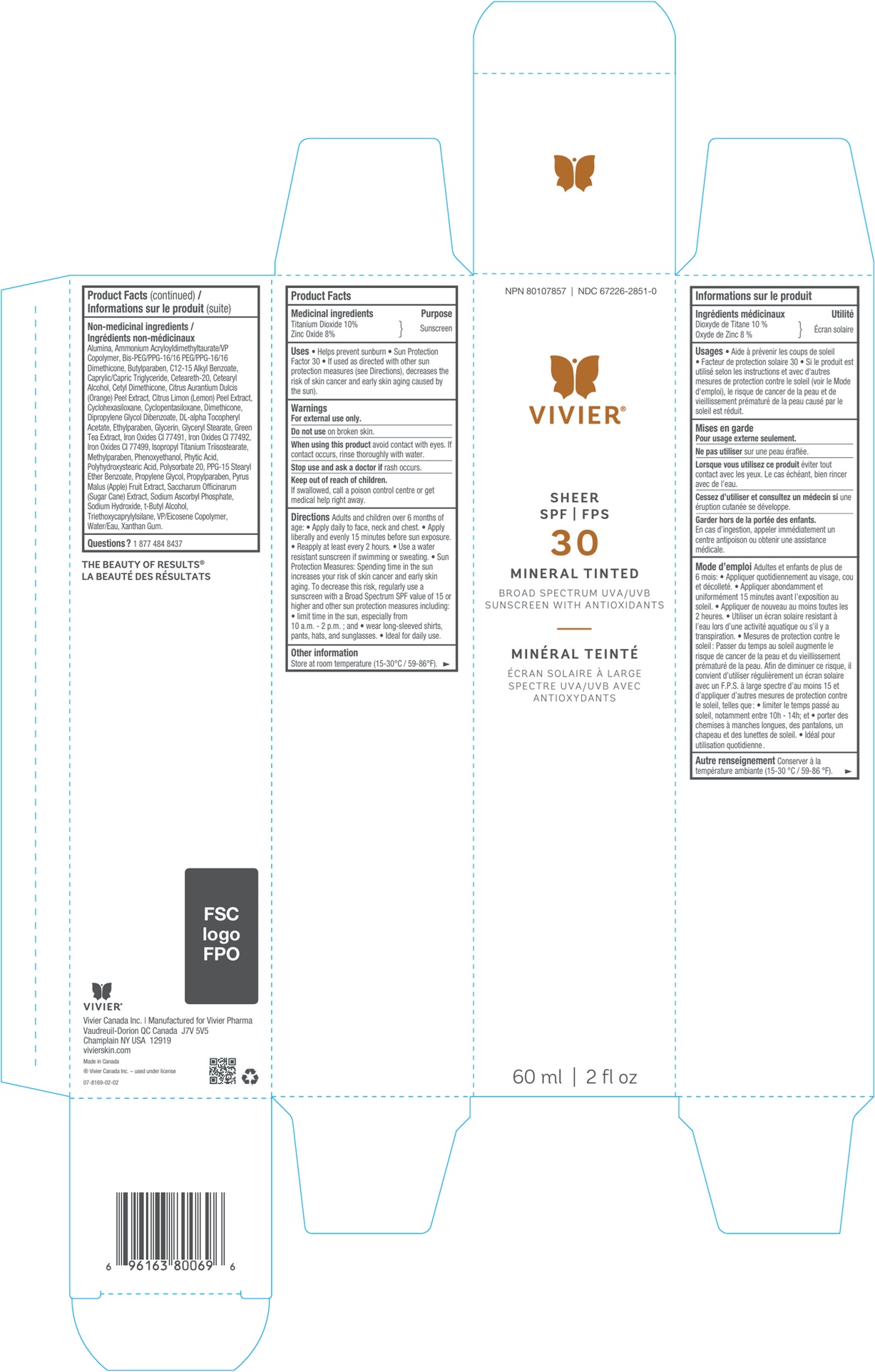 DRUG LABEL: Vivier Sheer SPF 30 Mineral Tinted
NDC: 67226-2851 | Form: LOTION
Manufacturer: Vivier Pharma, Inc.
Category: otc | Type: HUMAN OTC DRUG LABEL
Date: 20250505

ACTIVE INGREDIENTS: TITANIUM DIOXIDE 100 mg/1 mL; ZINC OXIDE 80 mg/1 mL
INACTIVE INGREDIENTS: ISOPROPYL TITANIUM TRIISOSTEARATE; METHYLPARABEN; PHENOXYETHANOL; ALUMINUM OXIDE; AMMONIUM ACRYLOYLDIMETHYLTAURATE/VP COPOLYMER; BIS-PEG/PPG-16/16 PEG/PPG-16/16 DIMETHICONE; BUTYLPARABEN; ALKYL (C12-15) BENZOATE; MEDIUM-CHAIN TRIGLYCERIDES; POLYOXYL 20 CETOSTEARYL ETHER; CETOSTEARYL ALCOHOL; ORANGE PEEL; LEMON PEEL; CYCLOMETHICONE 6; CYCLOMETHICONE 5; DIMETHICONE; DIPROPYLENE GLYCOL DIBENZOATE; .ALPHA.-TOCOPHEROL ACETATE, DL-; ETHYLPARABEN; GLYCERIN; GLYCERYL MONOSTEARATE; GREEN TEA LEAF; FERRIC OXIDE RED; FERRIC OXIDE YELLOW; FERROSOFERRIC OXIDE; FYTIC ACID; POLYSORBATE 20; PPG-15 STEARYL ETHER BENZOATE; PROPYLENE GLYCOL; PROPYLPARABEN; APPLE; SUGARCANE; SODIUM ASCORBYL PHOSPHATE; SODIUM HYDROXIDE; TERT-BUTYL ALCOHOL; TRIETHOXYCAPRYLYLSILANE; WATER; XANTHAN GUM

Vivier Sheer SPF 30 Mineral Tinted

Active ingredients (w/w)

Titanium Dioxide 10% Zinc Oxide 8%

Purpose

Sun Protectant

Uses

• Helps prevent sunburn and provides a sun protection factor of 30. • If used as directed with other sun protection measures (see Directions), decreases the risk of skin cancer and early skin aging caused by the sun.

Warnings

For external use only.

Do not use

on broken skin.

When using this product

void contact with eyes. If contact occurs, rinse thoroughly with water.

Stop use and ask a doctor if

rash occurs.

Keep out of reach of children.

If swallowed, call a poison control centre or get medical help right away.

Directions

Adults and children over 6 months of age: • Apply daily to face, neck and chest. • Apply liberally and evenly 15 minutes before sun exposure. • Reapply at least every 2 hours. • Use a water resistant sunscreen if swimming or sweating. • Sun Protection Measures: Spending time in the sun increases your risk of skin cancer and early skin aging. To decrease this risk, regularly use a sunscreen with a Broad Spectrum SPF value of 15 or higher and other sun protection measures including: • limit time in the sun, especially from 10 a.m. - 2 p.m. ; and • wear long-sleeved shirts, pants, hats, and sunglasses. • Ideal for daily use.

Other information

Store at room temperature (15-30°C / 59-86°F).

Non-medicinal ingredients

Alumina, Ammonium Acryloyldimethyltaurate/VP Copolymer, Bis-PEG/PPG-16/16 PEG/PPG-16/16 Dimethicone, Butylparaben, C12-15 Alkyl Benzoate, Caprylic/Capric Triglyceride, Ceteareth-20, Cetearyl Alcohol, Cetyl Dimethicone, Citrus Aurantium Dulcis (Orange) Peel Extract, Citrus Limon (Lemon) Peel Extract, Cyclohexasiloxane, Cyclopentasiloxane, Dimethicone, Dipropylene Glycol Dibenzoate, DL-alpha Tocopheryl Acetate, Ethylparaben, Glycerin, Glyceryl Stearate, Green Tea Extract, Iron Oxides CI 77491, Iron Oxides CI 77492, Iron Oxides CI 77499, Isopropyl Titanium Triisostearate, Methylparaben, Phenoxyethanol, Phytic Acid, Polyhydroxystearic Acid, Polysorbate 20, PPG-15 Stearyl Ether Benzoate, Propylene Glycol, Propylparaben, Pyrus Malus (Apple) Fruit Extract, Saccharum Officinarum (Sugarcane) Extract, Sodium Ascorbyl Phosphate, Sodium Hydroxide, t-Butyl Alcohol, Triethoxycaprylylsilane, VP/Eicosene Copolymer, Water/Eau, Xanthan Gum.

Questions?

1 877 484 8437